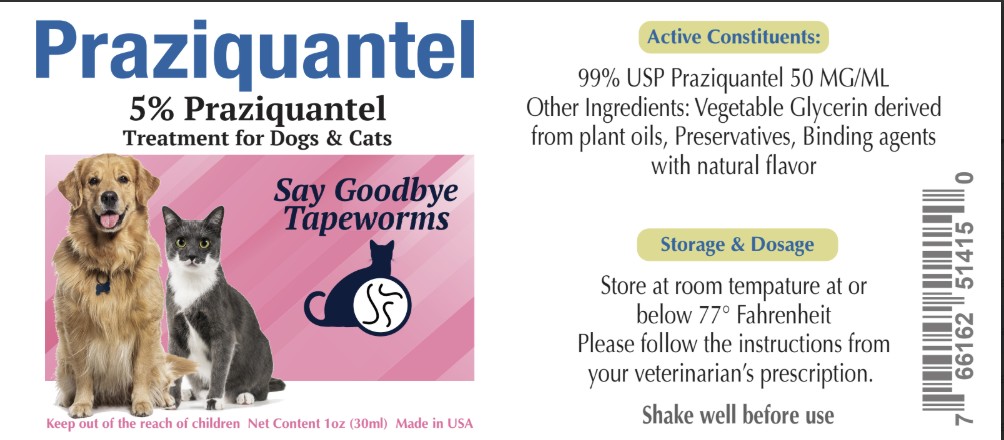 DRUG LABEL: Praziquantel
NDC: 86213-661 | Form: SUSPENSION
Manufacturer: Vetr LLC
Category: animal | Type: OTC ANIMAL DRUG LABEL
Date: 20250417

ACTIVE INGREDIENTS: PRAZIQUANTEL 50 mg/1 mL
INACTIVE INGREDIENTS: GLYCERIN; METHYLPARABEN; PROPYLPARABEN

Vetr Praziquantel, 5% Oral Suspension

Caution

Shake well before use. Solely for use under the guadance of your veterinarian. Follow dosing instructions from your veterinarian.

Active Ingredients

Praziquantel USP, 50 mg/mL (5% w/v)

Other Ingredients

Certified vegetable glycerin, natural preservatives and binding agents.

Storage

Store at room temperature at or below 25 C (<77 F)

Directions

Solely for use under the guidance of your veterinarian. Please consult your veterinarian for dosing size, duration and readministration schedule.

Say goodbye to tapeworms. Made in the USA. Available in 30mL, 60mL, 120mL and 240mL sizes.

Solely for use inder the guidance of your veterinarian.